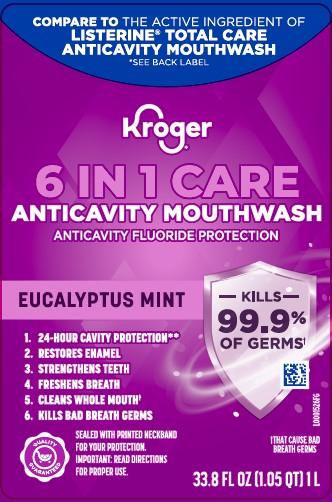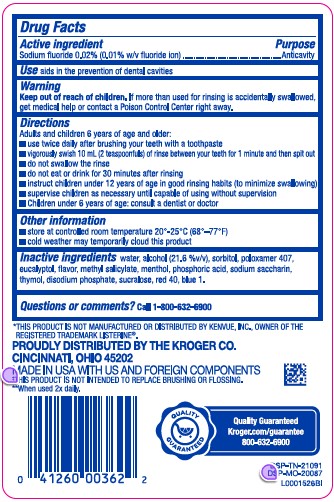 DRUG LABEL: Anticavity
NDC: 30142-163 | Form: MOUTHWASH
Manufacturer: The Kroger Co.
Category: otc | Type: HUMAN OTC DRUG LABEL
Date: 20260227

ACTIVE INGREDIENTS: SODIUM FLUORIDE 0.2 mg/1 mL
INACTIVE INGREDIENTS: WATER; ALCOHOL; SORBITOL; POLOXAMER 407; EUCALYPTOL; METHYL SALICYLATE; MENTHOL; PHOSPHORIC ACID; SACCHARIN SODIUM; THYMOL; SODIUM PHOSPHATE, DIBASIC, ANHYDROUS; SUCRALOSE; FD&C RED NO. 40; FD&C BLUE NO. 1

Kroger 163.005/163AF-AG
Anticavity Fluoride Rinse

Active Ingredient

Sodium Fluoride 0.02% W/V (0.01% fluoride ion)

Purpose

Anticavity

Use

aids in the prevention of dental cavities

Warning

for this product

Keep out of reach of children.

If more than used for rinsing is accidentally swallowed, get medical help or contact a Poison Control Center right away.

Directions

Adults and children 6 years of age and older

- use twice daily after brushing your teeth with a toothpaste
- vigorously swish 10 ml (2 teaspoonfuls) of rinse between your teeth for 1 minute then spit out
- do not swallow the rinse
- do not eat or drink for 30 minutes after rinsing
- instruct children under 12 years of age in good rinsing habits (to minimize swallowing)
- supervise children as necessary until capable of using without supervision
- children under 6 years of age: consult a dentist or doctor

Other information

• store at controlled room temperature 20⁰ - 25⁰C (68⁰ - 77⁰F)
• cold weather may temporarily cloud this product

Inactive ingredients

water, alcohol (21.6 %v/v), sorbitol, poloxamer 407, eucalyptol, flavor, methyl salicylate, menthol, phosphoric acid, sodium saccharin, thymol, disodium phosphate, sucralose, red 40, blue 1

Questions or Comments?

1-800-632-6900

Disclaimers

*THIS PRODUCT IS NOT MANUFACTURED OR DISTRIBUTED BY KENVUE, INC., OWNER OF THE REGISTERED TRADEMARK LISTERINE®.

**When used 2X daily

†THIS PRODUCT IS NOT INTENDED TO REPLACE BRUSHING OR FLOSSING.

Adverse Reactions

PROUDLY DISTRIBUTED BY THE KROGER CO.

CINCINNATI, OH 45202

MADE IN USA WITH DOMESTIC AND FOREIGN COMPONENTS

Quality Guaranteed

Kroger.com/guarantee

800-632-6900

DSP-TN-21091

DSP-MO-20087

principal display panel

COMPARE TO THE ACTIVE INGREDIENT OF LISTERINE® TOTAL CARE ANTICAVITY MOUTHWASH*

*SEE BACK LABEL

Kroger®

6 IN 1 CARE

ANTICAVITY MOUTHWASH

ANTICAVITY FLUORIDE PROTECTION

EUCALYPTUS MINT

1. 24HR CAVITY PROTECTION**
2. RESTORES ENAMEL
3. STRENGTHENS TEETH
4. FRESHENS BREATH
5. CLEANS WHOLE MOUTH†
6. KILLS BAD BREATH GERMS

KILLS 99.9% OF GERMS†

†THAT CAUSE BAD BREATH

QUALITY GUARANTEED

SEALED WITH PRINTED NECKBAND FOR YOUR PROTECTION.

IMPORTANT: READ DIRECTIONS FOR PROPER USE.

33.8 FL OZ (1.05 QT) 1 L